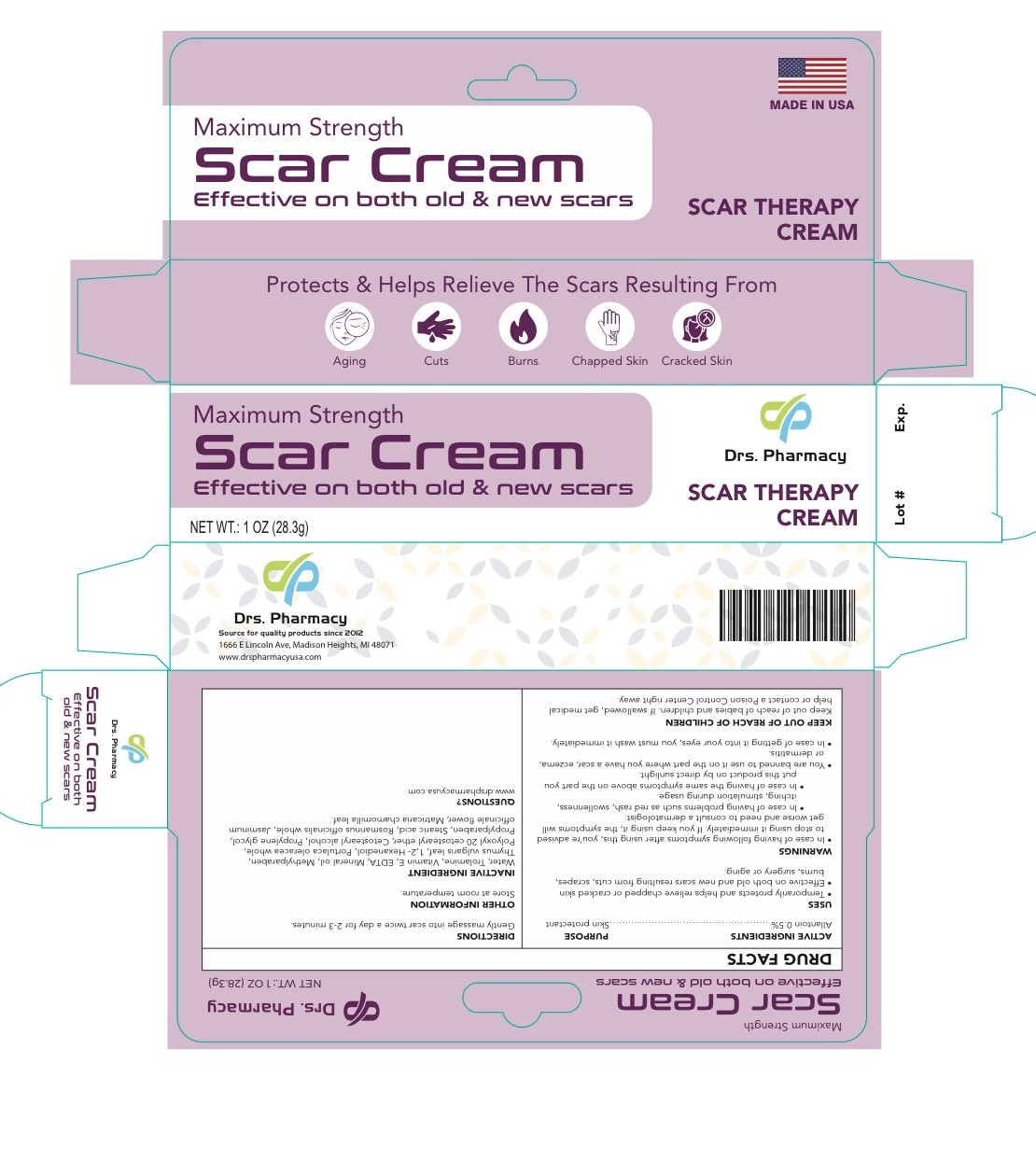 DRUG LABEL: Drs. pharmacy Scar Cream
NDC: 80489-333 | Form: CREAM
Manufacturer: OL PHARMA TECH, LLC Drs PHARMACY
Category: otc | Type: HUMAN OTC DRUG LABEL
Date: 20250109

ACTIVE INGREDIENTS: ALLANTOIN 0.5 g/100 g
INACTIVE INGREDIENTS: WATER; TROLAMINE; .ALPHA.-TOCOPHEROL; EDETATE DISODIUM; CETOSTEARYL ALCOHOL; PROPYLENE GLYCOL; STEARIC ACID; MINERAL OIL; METHYLPARABEN; THYMUS VULGARIS LEAF; 1,2-HEXANEDIOL; JASMINUM OFFICINALE FLOWER; MATRICARIA CHAMOMILLA LEAF; ROSMARINUS OFFICINALIS WHOLE; PORTULACA OLERACEA WHOLE; POLYOXYL 20 CETOSTEARYL ETHER; PROPYLPARABEN

ACTIVE INGREDIENT

Allantoin 0.5%

Dosage and Administration: Gently massage into scar twice a day for 2-3 minutes

Purpose: Skin Protectant

INDICATIONS AND USAGE

Indication and Usage: Temporarily protects and helps relieve chapped or cracked skin.

Inactive Ingredients

Cetostearyl alcohol- mineral oil- ceteareth 20- propylene glycol- methyl paraben- propylparaben- vitamin E- Stearic acid - trolamine RosmarinusOfficinalis (Rosemary)Extract/ Portulaca Oleracea Extract/Thymus Vulgaris Thyme) Leaf Extract/Jasminum Officinale (jasmine) Flower/ Leaf Extract?Chamomila) Recutita (Matricaria) Flower Water, Aureobasidium Pullulans Ferment Extract/ 1.2-Hexanedio

Warnings

- In case of having the following symptoms after using this cream, you are advised to stop using it immediately. If you keep using it , the symptoms will get worse and need to consult a drematologist .1- in case of having problems such as red rash, swollllenness, itching, stimulation during usage. 2- in case of having the same symptoms above on the part you put this product on by direct sunlight
- you are banned to use it on the part where you have a eczema, lor dermatitis.
- in case of getting it into your eyes, you have to wash it immediately.

Questions

drspharmacy.com

Keep out of reach of children and babies